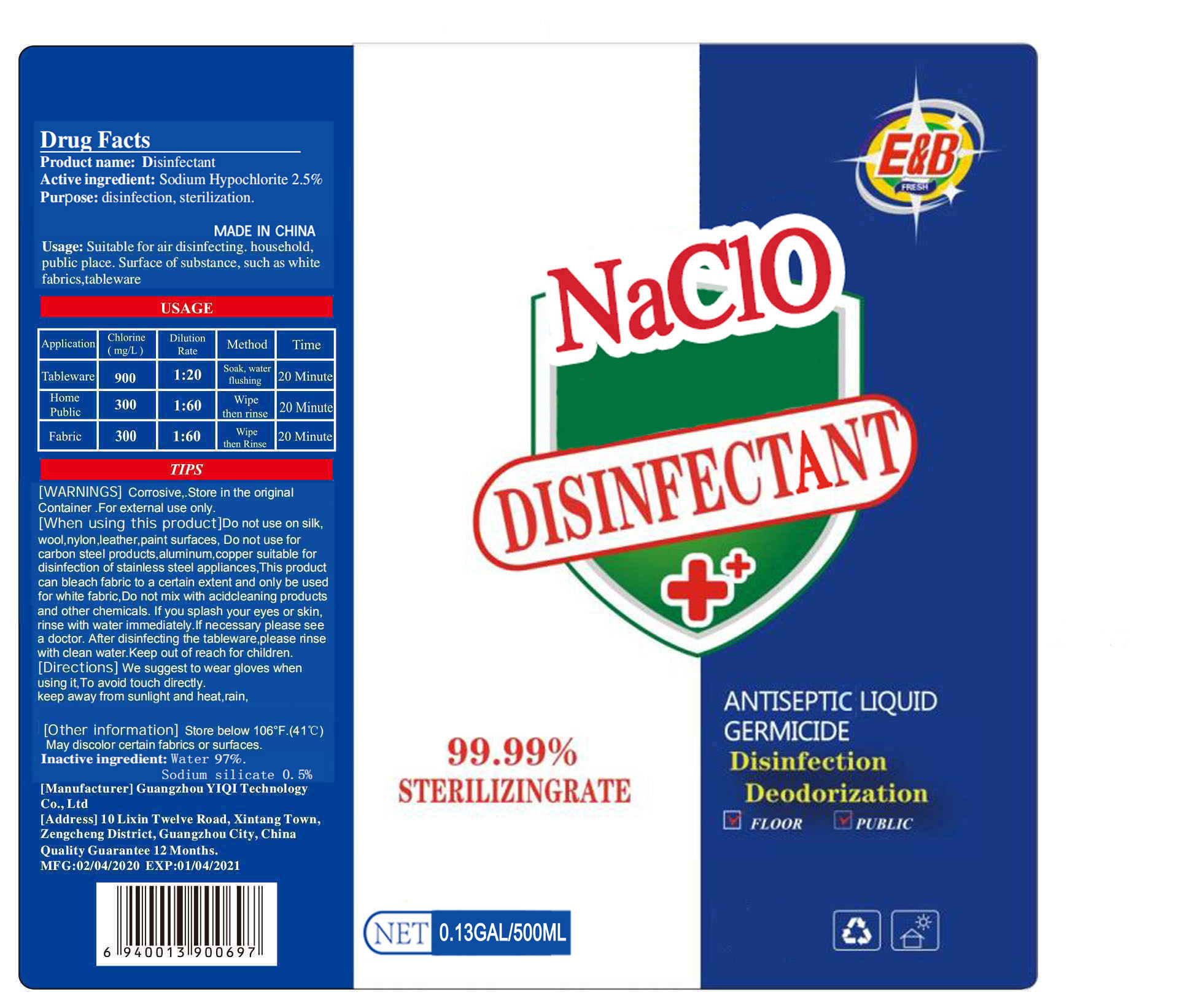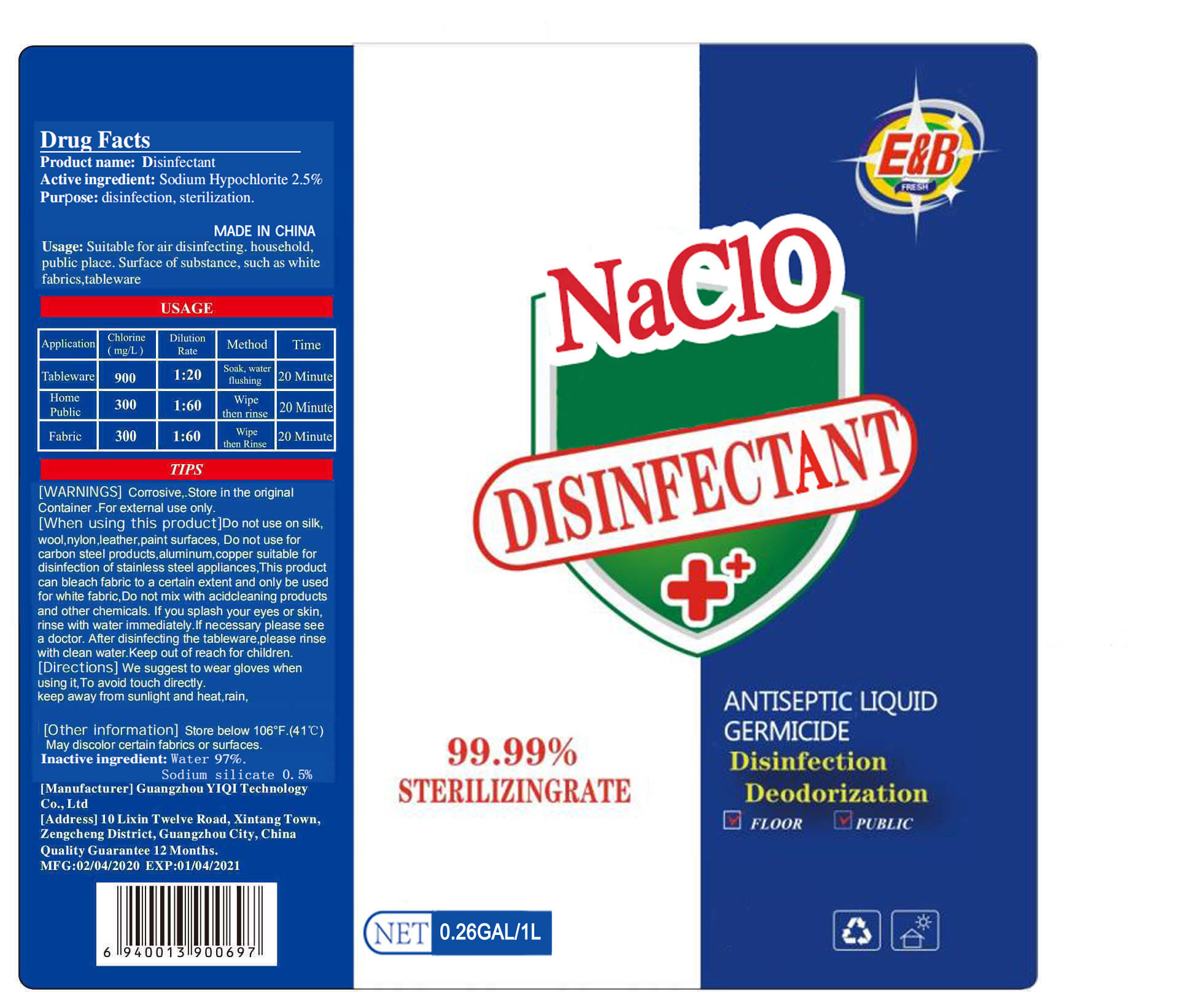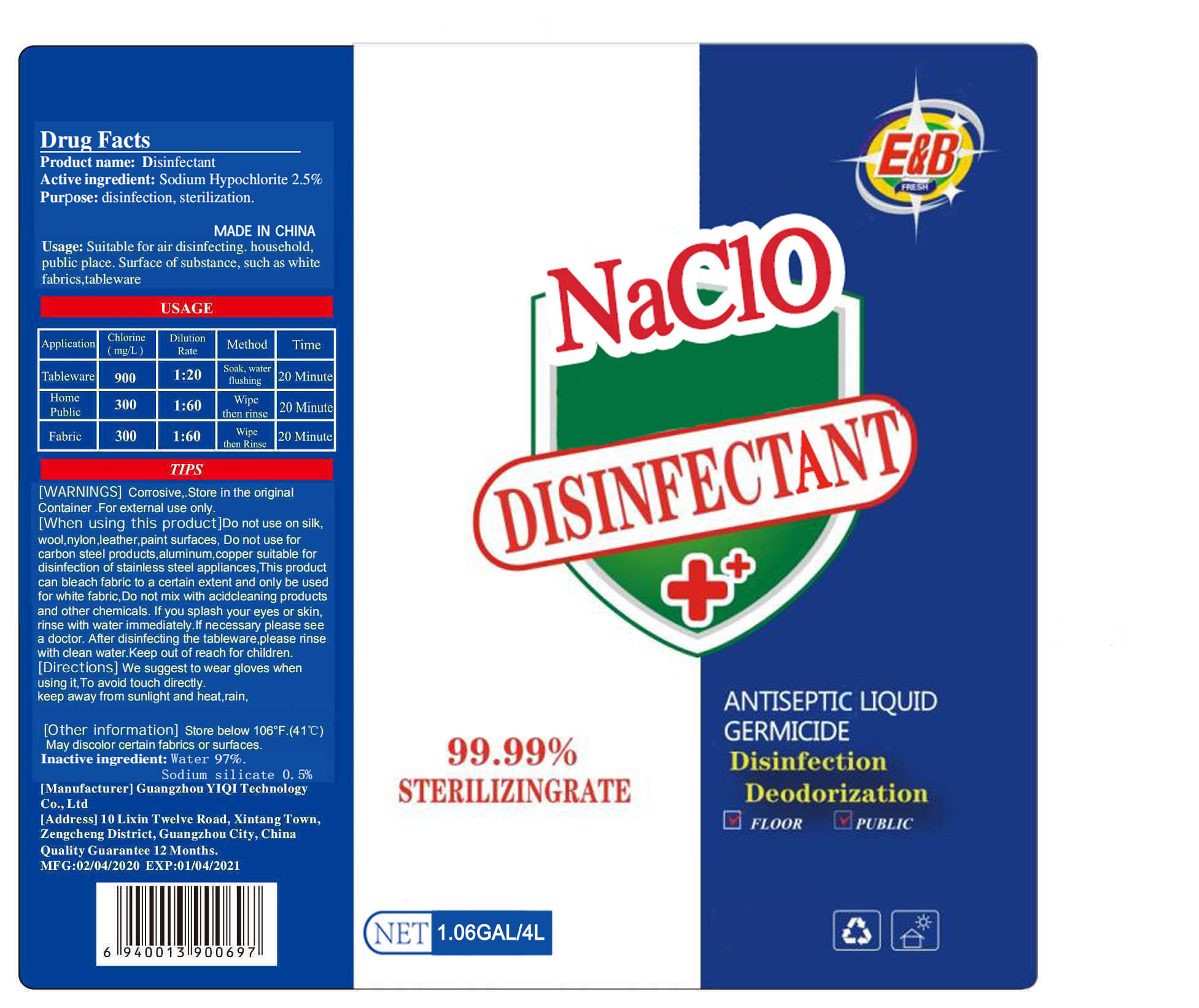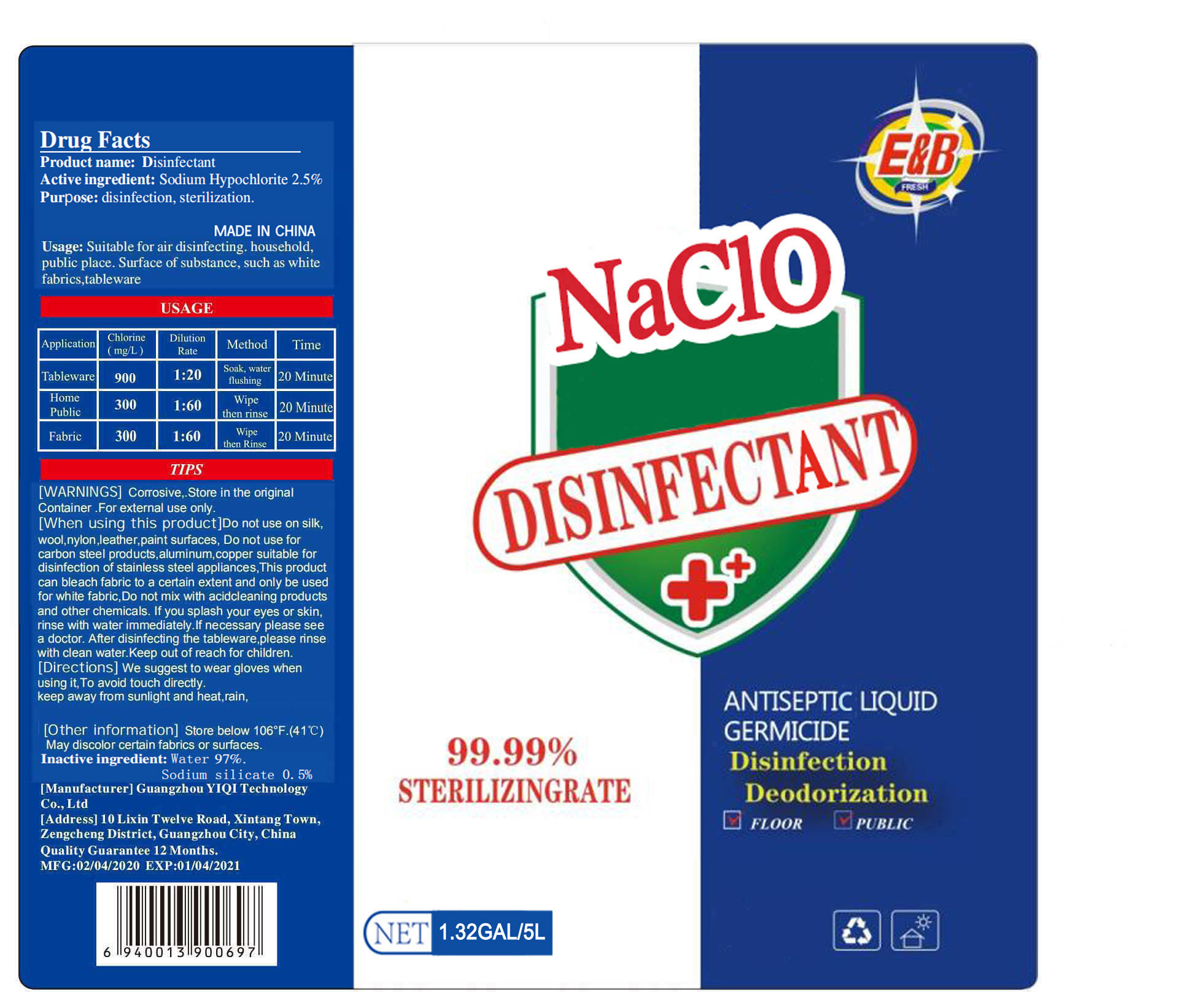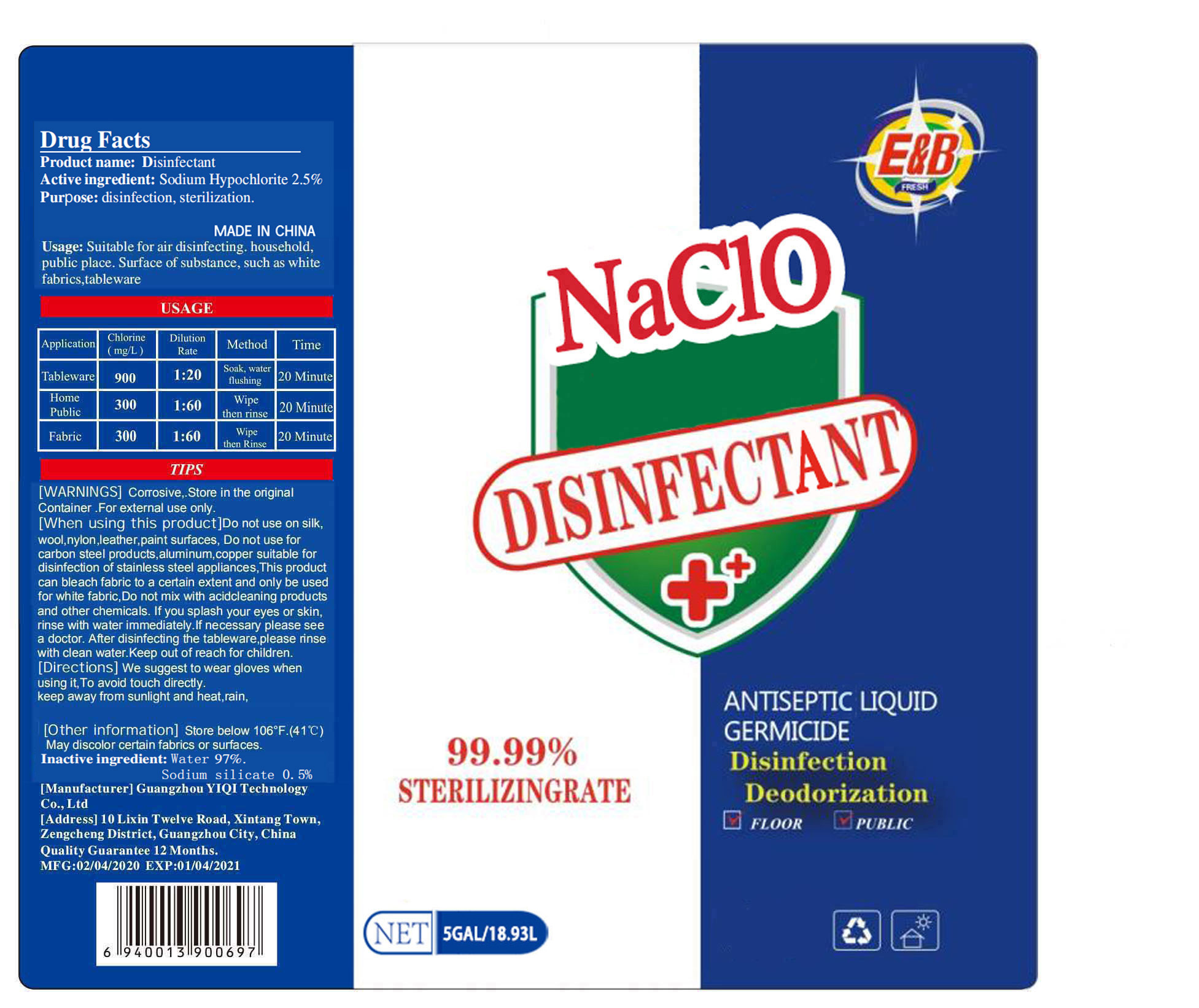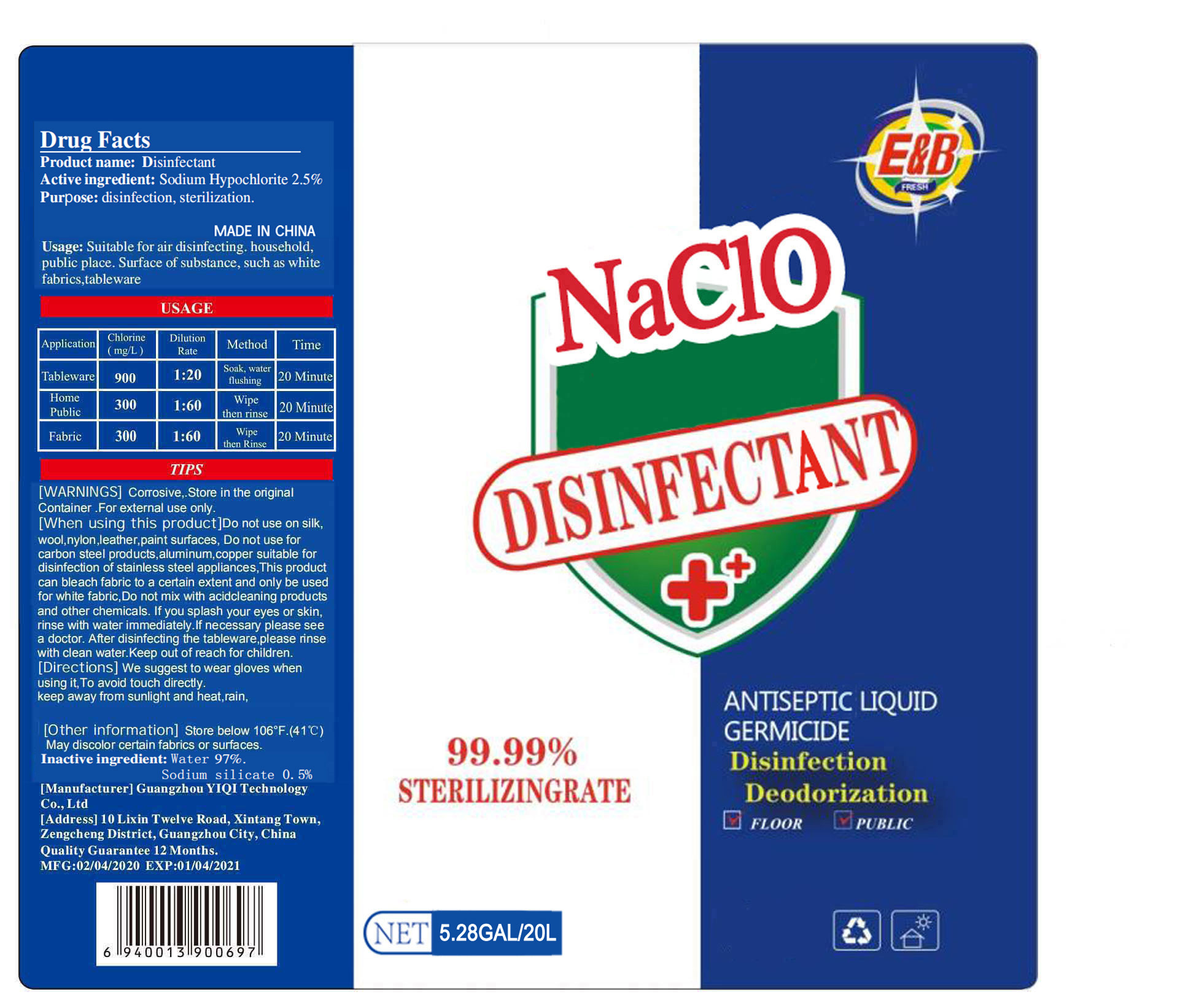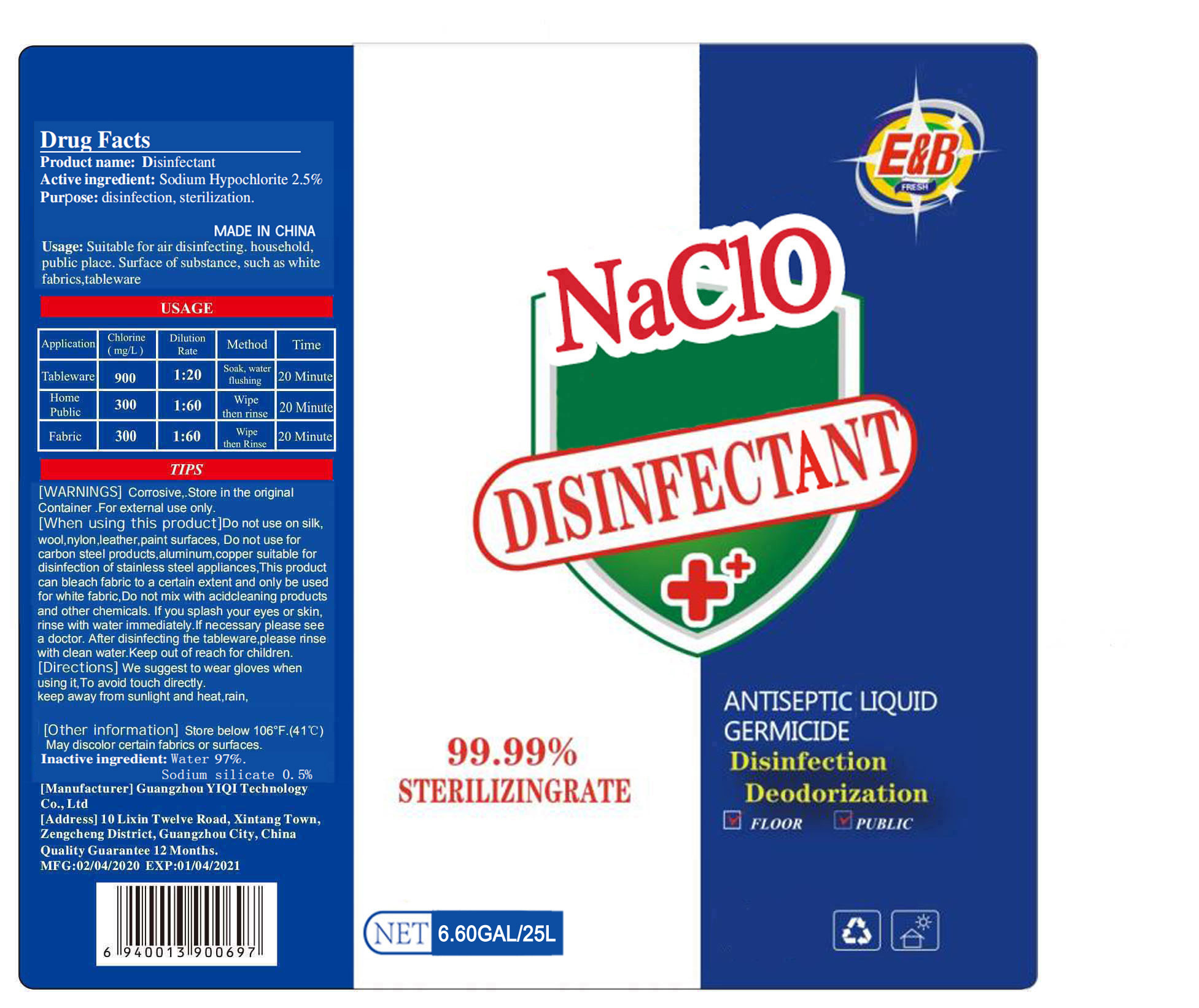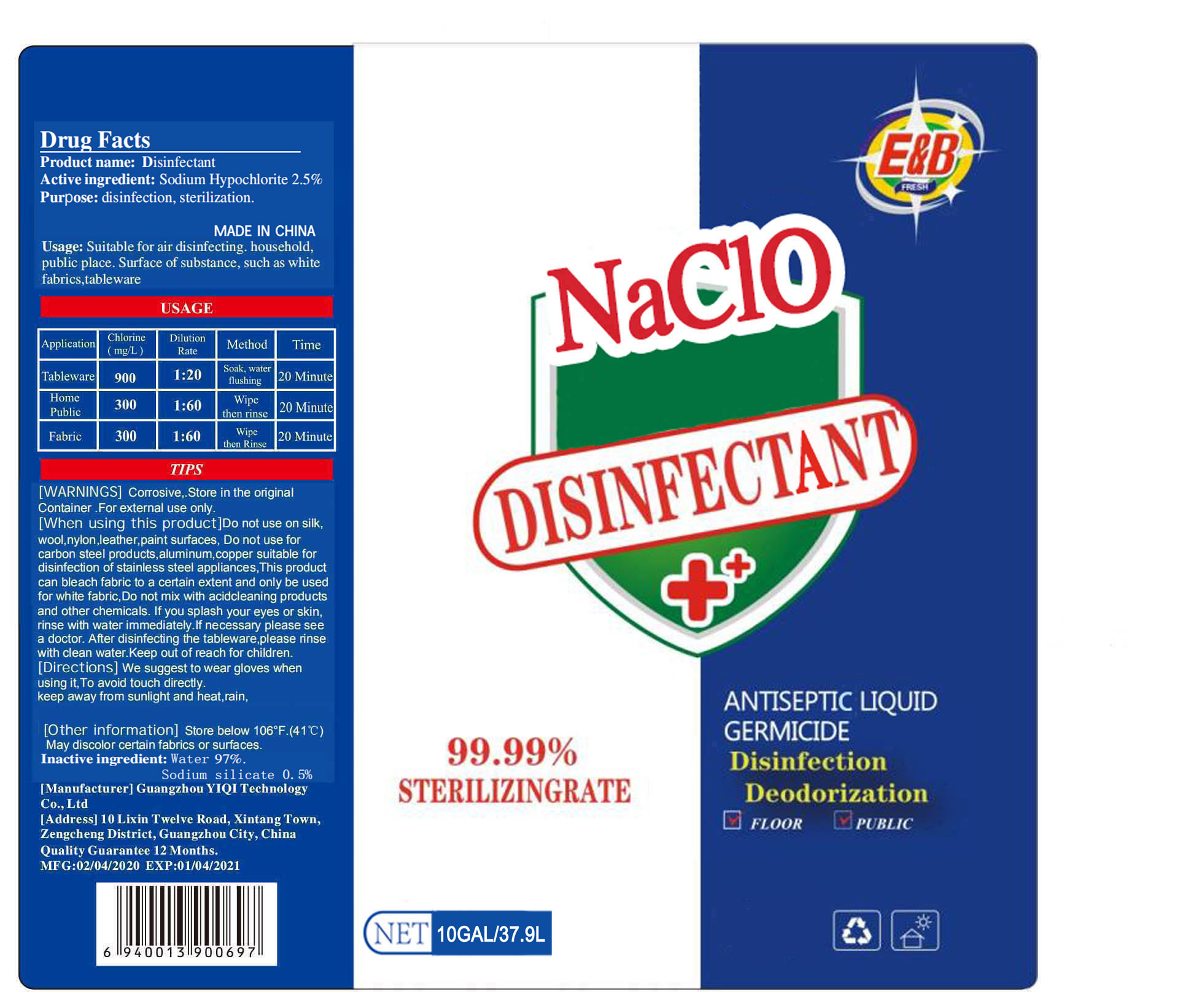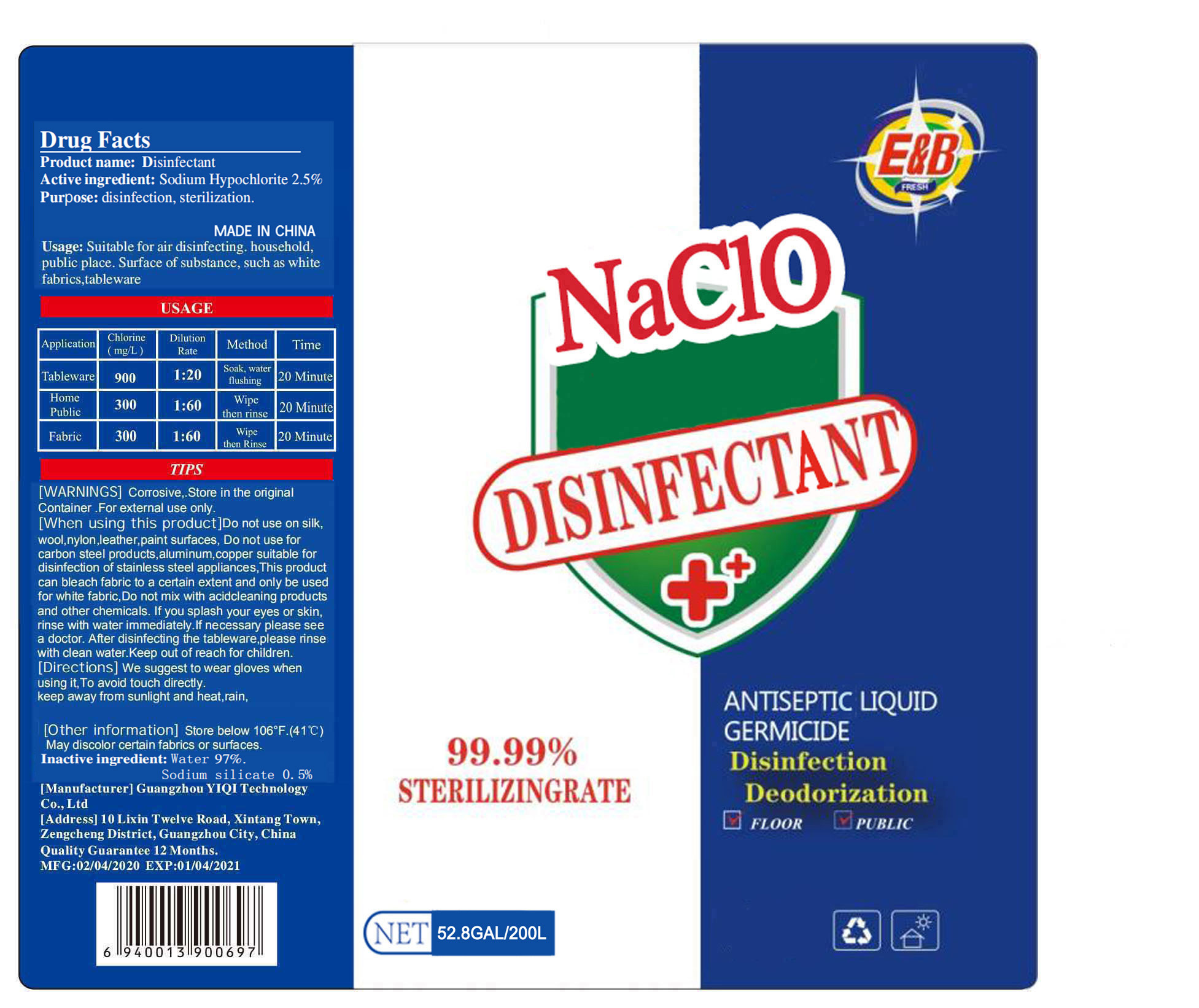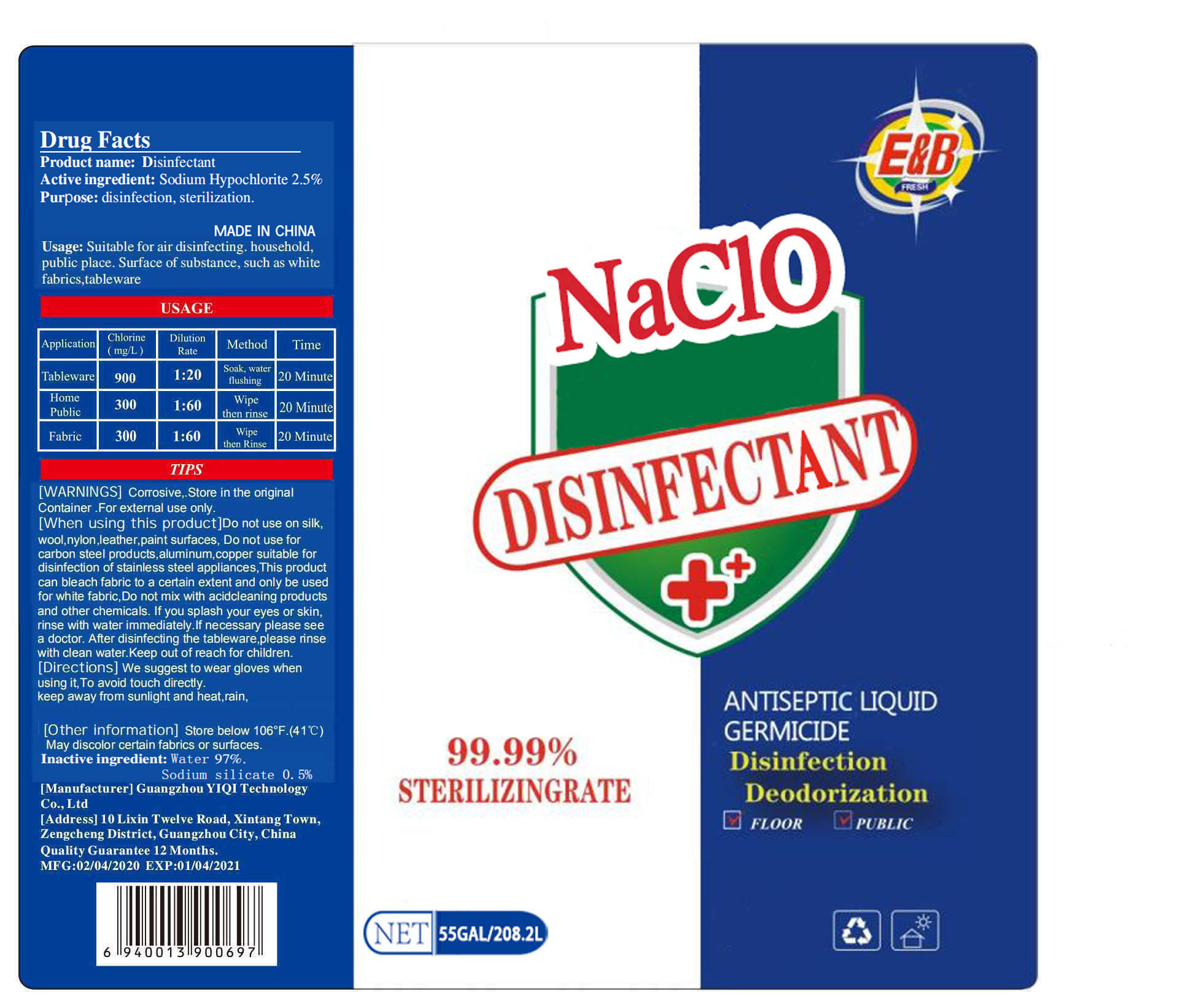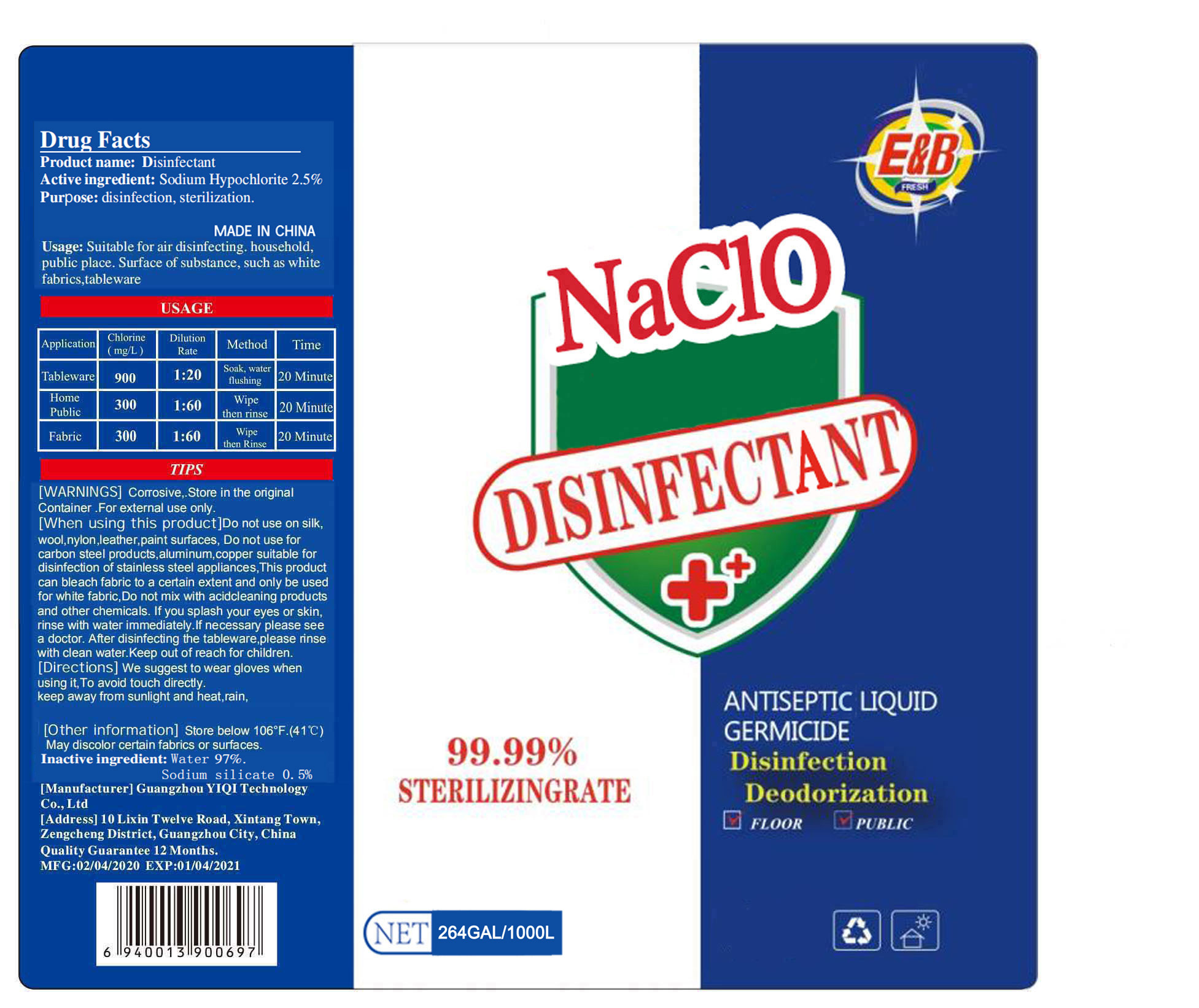 DRUG LABEL: Disinfectant
NDC: 78295-008 | Form: LIQUID
Manufacturer: GUANGZHOU YIQI TECHNOLOGY CO.,LTD
Category: otc | Type: HUMAN OTC DRUG LABEL
Date: 20201215

ACTIVE INGREDIENTS: SODIUM HYPOCHLORITE 2.5 kg/100 L
INACTIVE INGREDIENTS: WATER; SODIUM SILICATE

78295-008
Disinfectant

Active ingredient

Activeingredient：Sodium Hypochlorite 2.5%

Purpose

Purpose：disinfection， sterilization.

WARNINGS

Corrosive， .Store in the orginal Container.For external use only.

INDICATIONS AND USAGE

Usage:Suitable for air disinfecting.household, public place.Surface of substance, such as white fabrics, tableware

Application | Chlorine(mg/L) | Dilution Rate | method | Time
Tableware | 900 | 1:20 | Soak, water flushing | 20 Minute
Home Public | 300 | 1:60 | Wipe then rinse | 20 Minute
Fabric | 300 | 1:60 | wipc then rinse | 20 Minute

DO NOT USE

/

When using this product

Do not use on sik，wool， nylon， leather， paint surfaces， Do not use for carbon steel products， aluminum， copper suitable for disinfection of stainless steel appliances， This product can bleach fabric to a certain extent and only be used for white fabric， Do not mix with acid cleaning products and other chemicals.If you splash your eyes or skin，rinse with water immediately.If necessary please see a doctor.After disinfecting the tableware， please rinse with clean water.Keep out of reach for children.

STOP USE

/

KEEP OUT OF REACH OF CHILDREN

/

Directions

We suggest to wear gloves when using it To avoid touch directly. keep away from sunlight and heat， rain，

Other information

Store below 106°F.(41C)
May discolor certain fabrics or surfaces.

Inactive ingredient

Water97%. Sodium silicate 0.5%